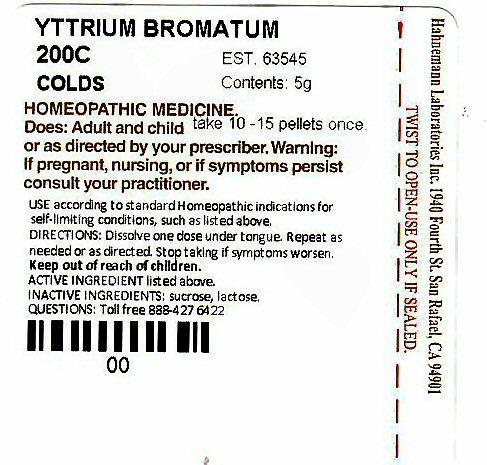 DRUG LABEL: HAHNEMANN COLDS
NDC: 63545-645 | Form: PELLET
Manufacturer: Hahnemann Laboratories, Inc. dba Alpine Pharmaceuticals
Category: homeopathic | Type: HUMAN OTC DRUG LABEL
Date: 20120114

ACTIVE INGREDIENTS: YTTRIUM BROMIDE 200 [hp_C]/1 1
INACTIVE INGREDIENTS: SUCROSE; LACTOSE

Active Ingredient

YTTRIUM BROMATUM

Purpose

COLDS

Keep Out Of Reach Of Children

Use

USE according to standard Homeopathic indications for self-limiting conditions, such as listed above. COLDS

Warnings

Warning: If pregnant, nursing, or if symptoms persist consult your practitioner.

Directions

DIRECTIONS: Dissolve one dose under tongue. Repeat as needed or as directed. Stop taking if symptoms worsen.
DOSE: Adults and children take 10 -15 pellets once or as directed by your prescriber.

Inactive Ingredients

INACTIVE INGREDIENTS: sucrose. lactose

Package Label

YTTRIUM BROMATUM 200C COLDS EST 63545 Contains 5g
HOMEOPATHIC MEDICINE
Hahnemann Laboratories Inc. 1940 Fourth St. San Rafael, CA 94901
TWIST TO OPEN-USE ONLY IF SEALED
QUESTIONS: Toll free 888-427-6422